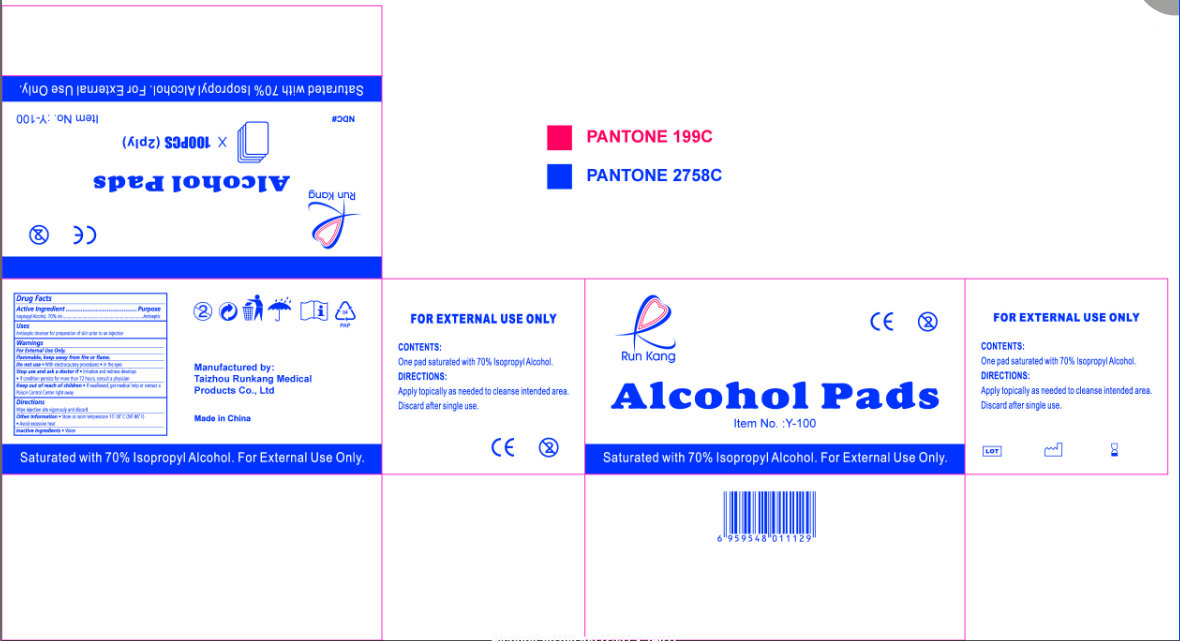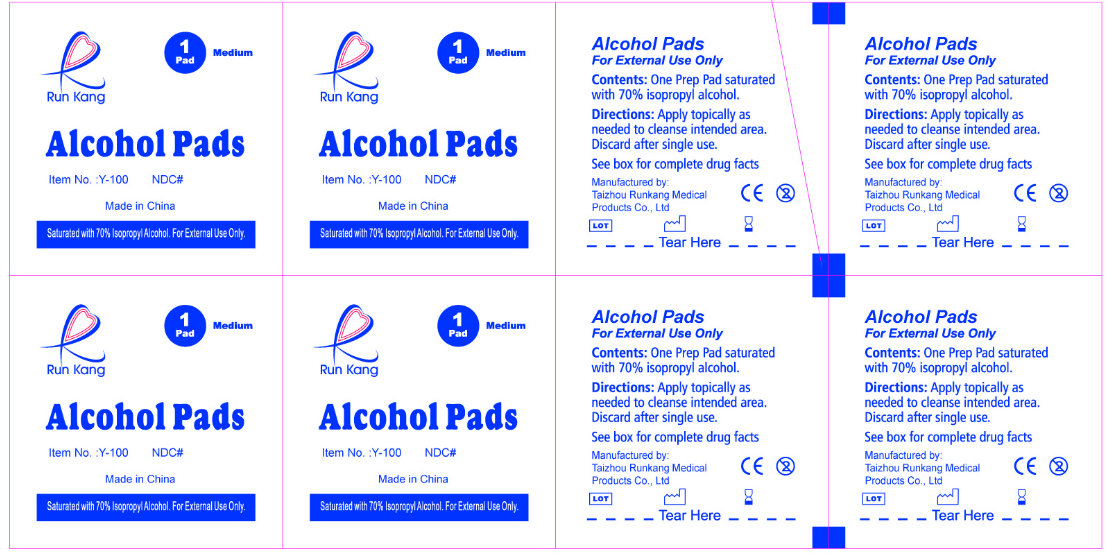 DRUG LABEL: Run Kang Alcohol Pads - MEDIUM
                
NDC: 57775-001 | Form: LIQUID
Manufacturer: Taizhou Runkang Medical Products Co.,Ltd.
Category: otc | Type: HUMAN OTC DRUG LABEL
Date: 20130408

ACTIVE INGREDIENTS: ISOPROPYL ALCOHOL 70 g/100 g
INACTIVE INGREDIENTS: WATER

Run Kang Alcohol Pads - MEDIUM

Active Ingredient

Isopropyl Alcohol, 70% v/v

Purpose

Antiseptic

Uses

- Antiseptic cleanser for preparation of skin prior to an injection

Warnings

For External Use Only.
Flammable, keep away from fire or flame.

Do not use

- With electrocautery procedures
- In the eyes.

Stop use and ask a doctor if

- Irritation and redness develops
- If condition persists for more than 72 hours, consult a physician

Keep out of reach of children.

If swallowed, get medical help or contact a Poison Control Center right away.

Directions

- Wipe injection site vigorously and discard

Other information

- Store at room temperature 15o - 30o C (59o - 86o F)
- Avoid excessive heat

Inactive Ingredients

Water

Run Kang Alcohol Pads

Manufactured by:
Taizhou Runkang Medical Products Co., Ltd.
Made in China
Saturated with 70% Isopropyl Alcohol. For External Use Only.
CONTENTS:
One pad saturated with 70% Isopropyl Alcohol.

PACKAGE LABEL

Run Kang CE
Alcohol Pads
Item No. :Y-100
Saturated with 70% Isopropyl Alcohol. For External Use Only.